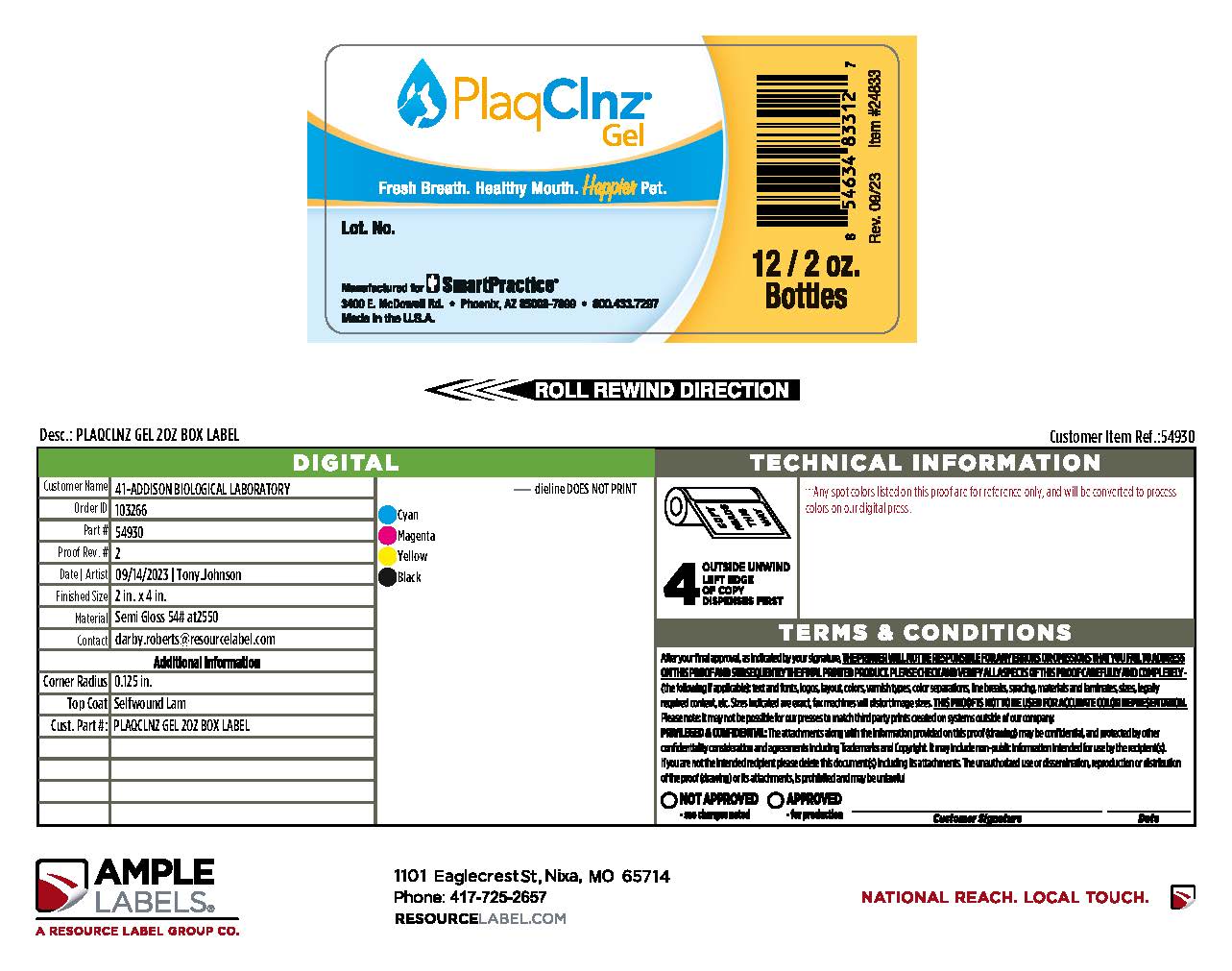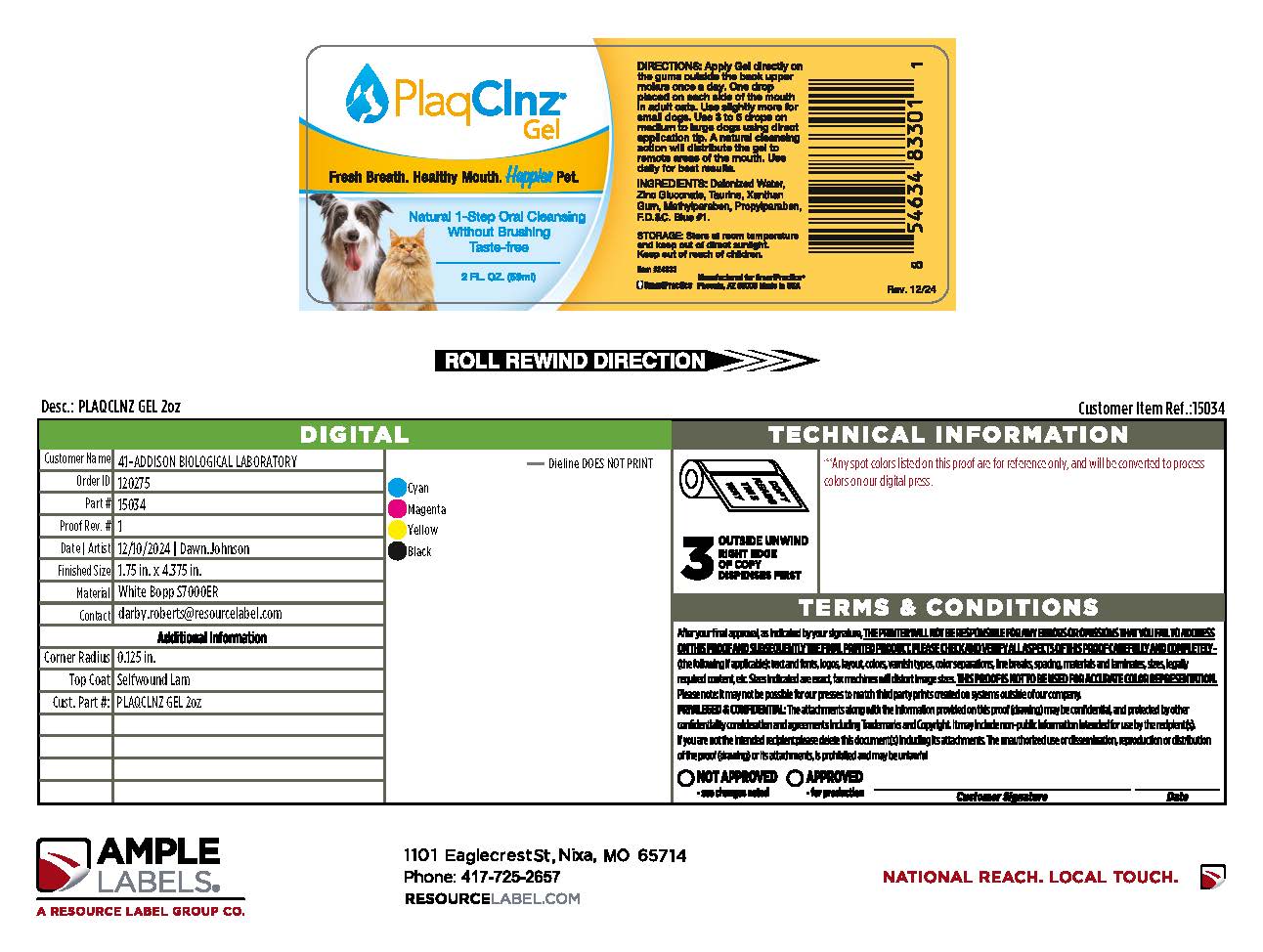 DRUG LABEL: PlaqClnz
NDC: 69521-006 | Form: GEL
Manufacturer: SmartHealth, Inc. (DBA SmartPratice)
Category: animal | Type: OTC ANIMAL DRUG LABEL
Date: 20251224

ACTIVE INGREDIENTS: ZINC GLUCONATE 0.022 g/1 mL
INACTIVE INGREDIENTS: WATER; TAURINE; METHYLPARABEN; FD&C BLUE NO. 1; PROPYLPARABEN; XANTHAN GUM

PlaqClnz® Gel

DOSAGE AND ADMINISTRATION

DIRECTIONS: Apply Gel directly on the gums outside the back upper molars once a day.One drop placed on each side of the mouth in adult cats.Use slightly more for small dogs.Use 3 to 5 drops on medium to large dogs using direct application tip. A natural cleansing action will distribute the gel to remote areas of the mouth. Use daily for best results.

INGREDIENTS: Deionized Water, Zinc Gluconate, Taurine, Xanthan Gum, Methylparaben, Propylparaben, F.D.&C. Blue#1.

STORAGE AND HANDLING

STORAGE: Store at room temperature and keep out of direct sunlight.

Keep out of reach of children.

Item #24833

Manufactured for SmartPractice

SmartPractice Phoenix, AZ 85008 Made in USA Rev. 12/24

VIAL LABEL

PlaqClnz®
Gel

Fresh Breath. Healthy Mouth. Happier Pet.

Natural 1-Step Oral Cleansing
Without Brushing
Taste-free

2 FL. OZ. (59ml)

DIRECTIONS: Apply Gel directly on the gums outside the back upper molars once a day. One drop placed on each side of the mouth in adult cats. Use slightly more for small dogs. Use 3 to 5 drops on medium to large dogs using direct application tip. A natural cleansing action will distribute the gel to remote areas of the mouth. Use daily for best results.

INGREDIENTS: Deionized Water, Carboxymethylcellulose, Zinc Gluconate, Taurine, Methylparaben, Propylparaben, F.D.&C. Blue #1.

STORAGE: Store at room temperature and keep out of direct sunlight. Keep out of reach of children.

Item #24833

SmartPractice

Manufactured for SmartPractice®

BOX LABEL

PlaqClnz®
Gel

Fresh Breath. Healthy Mouth. Happier Pet.

Lot.No.

Manufactured for SmartPractice

3400 E.McDowell Rd . Phoenix,AZ 85008-7899 .800.433.7297

Made in the U.S.A

12/2oz.

Bottles

Rev 09.23 Item #24833